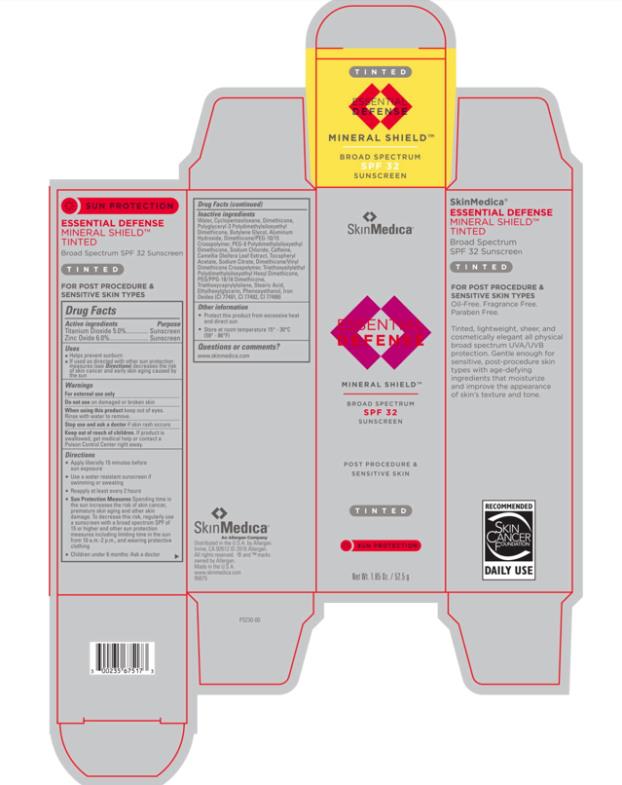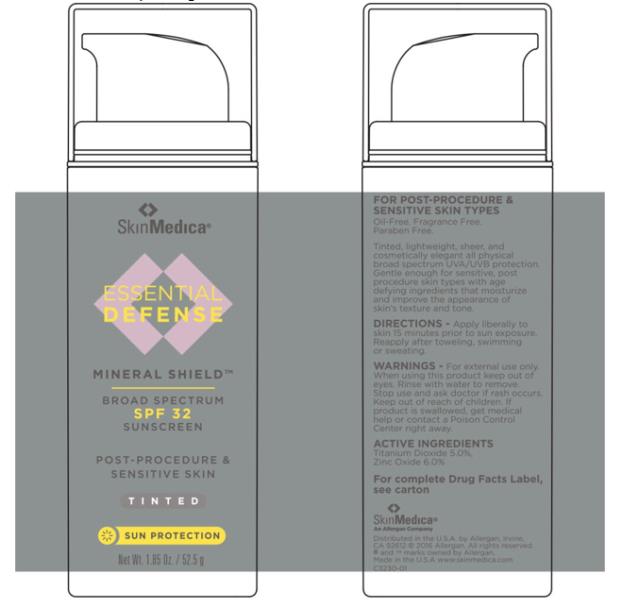 DRUG LABEL: Essential Defense Mineral Shield Broad Spectrum SPF 32 TINTED Sunscreen
NDC: 0023-5675 | Form: LOTION
Manufacturer: Allergan, Inc.
Category: otc | Type: HUMAN OTC DRUG LABEL
Date: 20190101

ACTIVE INGREDIENTS: Titanium Dioxide 50 mg/1 g; Zinc oxide 60 mg/1 g
INACTIVE INGREDIENTS: WATER; CYCLOMETHICONE 5; DIMETHICONE; POLYGLYCERYL-3 POLYDIMETHYLSILOXYETHYL DIMETHICONE (4000 MPA.S); BUTYLENE GLYCOL; ALUMINUM HYDROXIDE; SODIUM CHLORIDE; PEG-9 POLYDIMETHYLSILOXYETHYL DIMETHICONE; PHENOXYETHANOL; FERRIC OXIDE YELLOW; DIMETHICONE/VINYL DIMETHICONE CROSSPOLYMER (SOFT PARTICLE); SODIUM CITRATE, UNSPECIFIED FORM; PEG/PPG-18/18 DIMETHICONE; FERRIC OXIDE RED; ETHYLHEXYLGLYCERIN; CAMELLIA OLEIFERA LEAF; TRIETHOXYCAPRYLYLSILANE; .ALPHA.-TOCOPHEROL ACETATE; FERROSOFERRIC OXIDE; STEARIC ACID; CAFFEINE; DIMETHICONE/PEG-10/15 CROSSPOLYMER

Drug Facts

Active ingredients

Titanium Dioxide 5.0%

Zinc Oxide 6.0%

Purpose

Sunscreen

Sunscreen

Uses

- Helps prevent sunburn
- If used as directed with other sun protection measures (see Directions) decreases the risk of skin cancer and early skin aging caused by the sun

Warnings

For external use only

Do not use

on damaged or broken skin

When using this product

keep out of eyes. Rinse with water to remove.

Stop use and ask a doctor

if skin rash occurs

Keep out of reach of children.

If product is swallowed, get medical help or contact a Poison Control Center right away.

Directions

- Apply liberally 15 minutes before sun exposure
- Use a water resistant sunscreen if swimming or sweating
- Reapply at least every 2 hours
- Sun Protection Measures Spending time in the sun increases the risk of skin cancer, premature skin aging and other skin damage. To decrease this risk, regularly use a sunscreen with a broad spectrum SPF of 15 or higher and other sun protection measures including limiting time in the sun from 10 a.m.-2 p.m., and wearing protective clothing
- Children under 6 months: Ask a doctor

Inactive ingredients

Water, Cyclopentasiloxane, Dimethicone, Polyglyceryl-3 Polydimethylsiloxyethyl Dimethicone, Butylene Glycol, Aluminum Hydroxide, Dimethicone/PEG-10/15 Cross polymer, PEG-9 Polydimethylsiloxyethyl Dimethicone, Sodium Chloride, Caffeine, Camellia Oleifera Leaf Extract, Tocopheryl Acetate, Sodium Citrate, Dimethicone/Vinyl Dimethicone Crosspolymer, Triethoxvsilylethyl Polydimethylsiloxyethyl Hexyl Dimethicone, PEG/PPG-18/18 Dimethicone, Triethoxycaprylylsilane, Stearic Acid, Ethylhexylglycerin, Phenoxyethanol, Iron Oxides (CI 77491, CI 77492, CI 77499)

Other information

- Protect this product from excessive heat and direct sun
- Store at room temperature 15° - 30°C (59° - 86°F)

Questions or comments?

www.skinmedica.com

Principal Display Panel - Carton Label

SkinMedica®
ESSENTIAL
DEFENSE
MINERAL SHIELD™
BROAD SPECTRUM
SPF 32
SUNSCREEN
POST PROCEDURE &
SENSITIVE SKIN
TINTED
SUN PROTECTION
Net Wt. 1.85 Oz. / 52.5 g

Principal Display Panel - Tube Label

SkinMedica®
ESSENTIAL
DEFENSE
MINERAL SHIELD™
BROAD SPECTRUM
SPF 32
SUNSCREEN
POST-PROCEDURE &
SENSITIVE SKIN
TINTED
SUN PROTECTION
Net Wt. 1.85 Oz. / 52.5 g